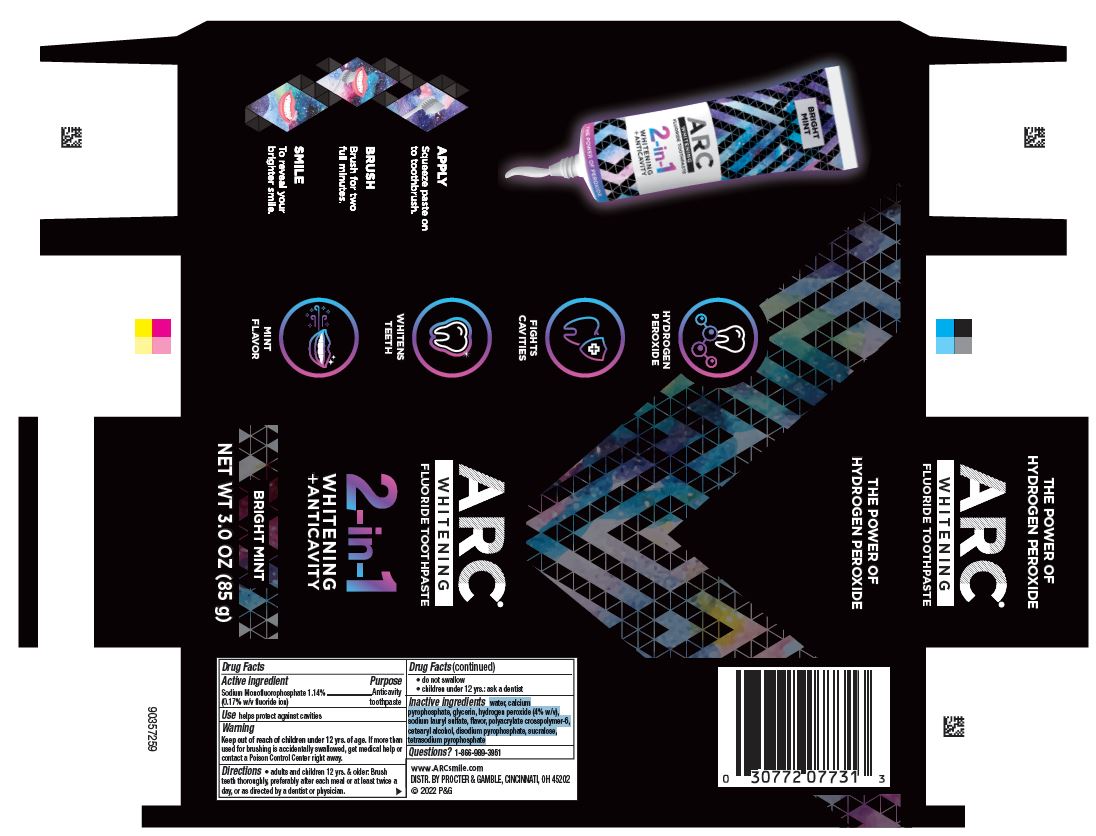 DRUG LABEL: ARC 2 in 1
NDC: 69423-837 | Form: PASTE, DENTIFRICE
Manufacturer: The Procter & Gamble Manufacturing Company
Category: otc | Type: HUMAN OTC DRUG LABEL
Date: 20250225

ACTIVE INGREDIENTS: SODIUM MONOFLUOROPHOSPHATE 1.7 mg/1 g
INACTIVE INGREDIENTS: CALCIUM PYROPHOSPHATE; AMMONIUM ACRYLOYLDIMETHYLTAURATE, DIMETHYLACRYLAMIDE, LAURYL METHACRYLATE AND LAURETH-4 METHACRYLATE COPOLYMER, TRIMETHYLOLPROPANE TRIACRYLATE CROSSLINKED (45000 MPA.S); CETOSTEARYL ALCOHOL; SODIUM PYROPHOSPHATE; GLYCERIN; HYDROGEN PEROXIDE; SODIUM LAURYL SULFATE; WATER; SUCRALOSE; SODIUM ACID PYROPHOSPHATE

Arc 2-in-1 Whitening + Anticavity

Drug Facts

Sodium monofluorophosphate 1.14%

(0.17% w/v fluoride ion)

Purpose

Anticavity toothpaste

Use

helps protect against cavities

Warning

Keep out of reach of children under 12 yrs. of age. If more than used for brushing is accidentally swallowed, get medical help or contact a Poison Control Center right away.

Directions

- adults and children 12 yrs. & older: Brush teeth thoroughly, preferably after each meal or at least twice a day, or as directed by a dentist or physician.
- do not swallow
- children under 12 yrs.: ask a dentist

Inactive ingredients

water, glycerin, calcium pyrophosphate,
hydrogen peroxide (4% w/v), sodium lauryl sulfate, flavor, polyacrylate
crosspolymer-6, cetearyl alcohol, disodium pyrophosphate, sucralose, tetrasodium
pyrophosphate

Questions?

1-866-989-3951

DISTR. BY PROCTER & GAMBLE, CINCINNATI, OH 45202

Crest 3D White Ultra White 85g tube in carton

THE POWER OF

HYDROGEN PEROXIDE

ARC

WHITENING

FLUORIDE TOOTHPASTE

2-in-1

WHITENING

+ ANTICAVITY

BRIGHT MINT

NET WT 3.0 OZ (85 g)